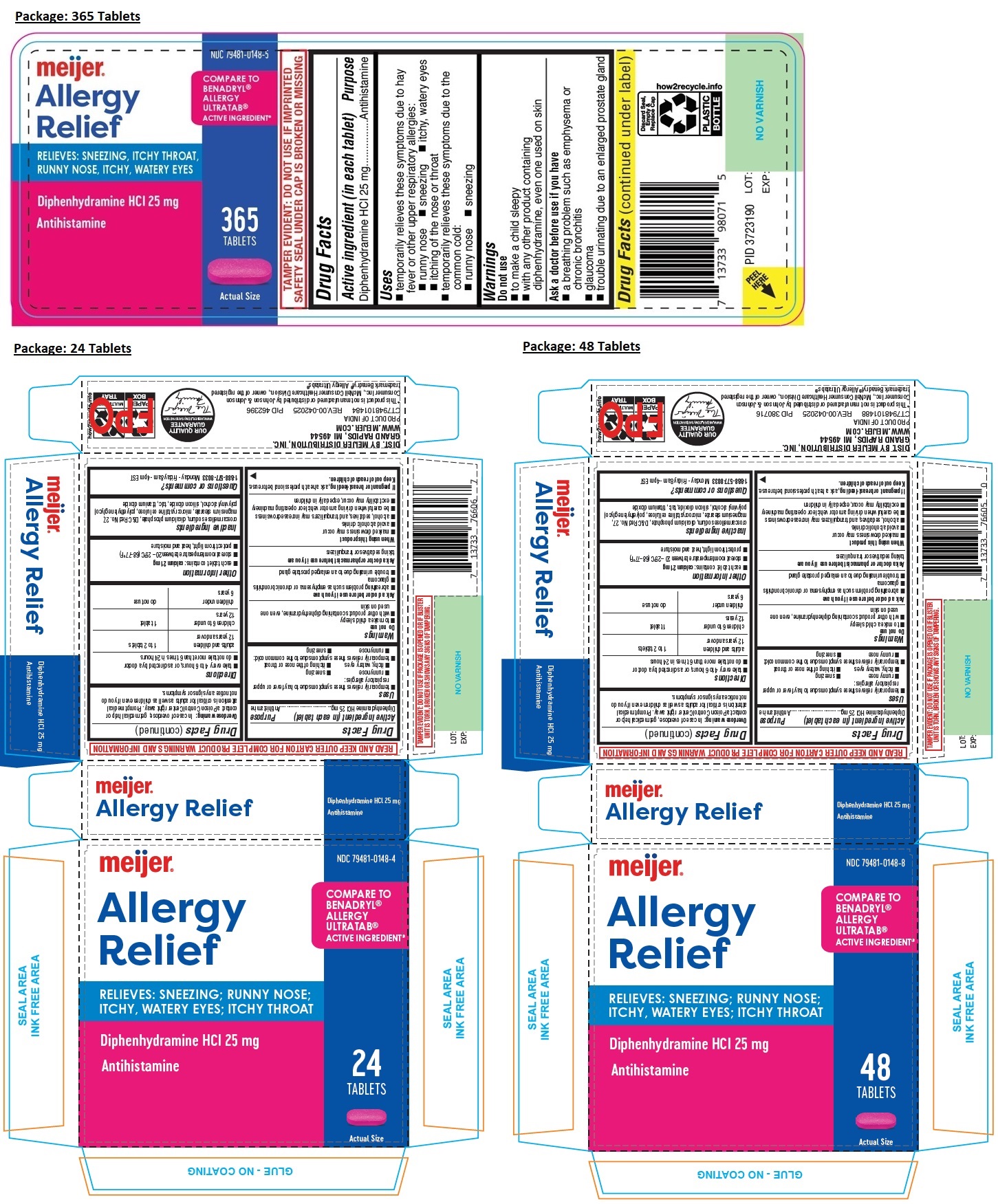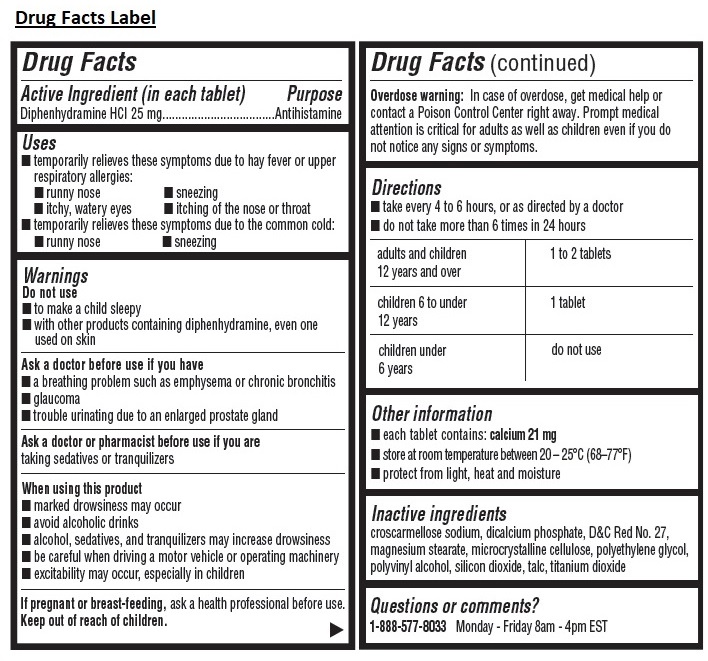 DRUG LABEL: meijer Allergy Relief
NDC: 79481-0148 | Form: TABLET
Manufacturer: Meijer, Inc.
Category: otc | Type: HUMAN OTC DRUG LABEL
Date: 20250418

ACTIVE INGREDIENTS: DIPHENHYDRAMINE HYDROCHLORIDE 25 mg/1 1
INACTIVE INGREDIENTS: CROSCARMELLOSE SODIUM; ANHYDROUS DIBASIC CALCIUM PHOSPHATE; D&C RED NO. 27; MAGNESIUM STEARATE; MICROCRYSTALLINE CELLULOSE; POLYETHYLENE GLYCOL, UNSPECIFIED; POLYVINYL ALCOHOL, UNSPECIFIED; SILICON DIOXIDE; TALC; TITANIUM DIOXIDE

meijer Allergy Relief

Active ingredient (in each tablet)

Diphenhydramine HCl 25 mg

Purpose

Antihistamine

Uses

• temporarily relieves these symptoms due to hay fever or other upper respiratory allergies:
• runny nose • sneezing • itchy, watery eyes • itching of the nose or throat
• temporarily relieves these symptoms due to the common cold:
• runny nose • sneezing

Warnings

Do not use
• to make a child sleepy
• with other productS containing diphenhydramine, even one used on skin

Ask a doctor before use if you have
• a breathing problem such as emphysema or chronic bronchitis
• glaucoma
• trouble urinating due to an enlarged prostate gland

Ask a doctor or pharmacist before use if you are taking sedatives or tranquilizers

When using this product
• marked drowsiness may occur
• avoid alcoholic drinks
• alcohol, sedatives, and tranquilizers may increase drowsiness
• be careful when driving a motor vehicle or operating machinery
• excitability may occur, especially in children

If pregnant or breast-feeding, ask a health professional before use.

Keep out of reach of children.
Overdose warning: In case of overdose, get medical help or contact a Poison Control Center right away. Prompt medical attention is critical for adults as well as children even if you do not notice any signs or symptoms.

Directions

• take every 4 to 6 hours, or as directed by a doctor
• do not take more than 6 times in 24 hours

adults and children 12 years and over | 1 to 2 tablets
children 6 to under 12 years | 1 tablet
children under 6 years | do not use

Other information

• each tablet contains: calcium 21 mg
• store at room temperature between 20-25°C (68-77°F)
• avoid excessive heat, cold and humidity
• close cap tightly after use
• protect from light, heat and moisture

Inactive ingredients

croscarmellose sodium, dicalcium phosphate, D&C red no. 27, magnesium stearate, microcrystalline cellulose, polyethylene glycol, polyvinyl alcohol, silicon dioxide, talc, titanium dioxide

Questions or comments?

1-888-577-8033 Monday - Friday 8am - 4pm EST

COMPARE TO BENADRYL ®ALLERGY ULTRATAB ®ACTIVE INGREDIENT*

TAMPER EVIDENT: DO NOT USE IF IMPRINTED SAFETY SEAL UNDER CAP IS BROKEN OR MISSING

TAMPER EVIDENT: DO NOT USE IF PACKAGE IS OPENED OR IF BLISTER UNIT IS TORN, BROKEN OR SHOWS ANY SIGNS OF TAMPERING.

READ AND KEEP OUTER CARTON FOR COMPLETE PRODUCT WARNINGS AND INFORMATION

DIST. BY MEIJER DISTRIBUTION, INC.
GRAND RAPIDS, MI 49544

WWW.MEIJER.COM

PRODUCT OF INDIA

*This product is not manufactured or distributed by Johnson & Johnson Consumer Inc., McNeil Consumer Healthcare Division., owner of the registered trademark Benadryl® Allergy Ultratabs®